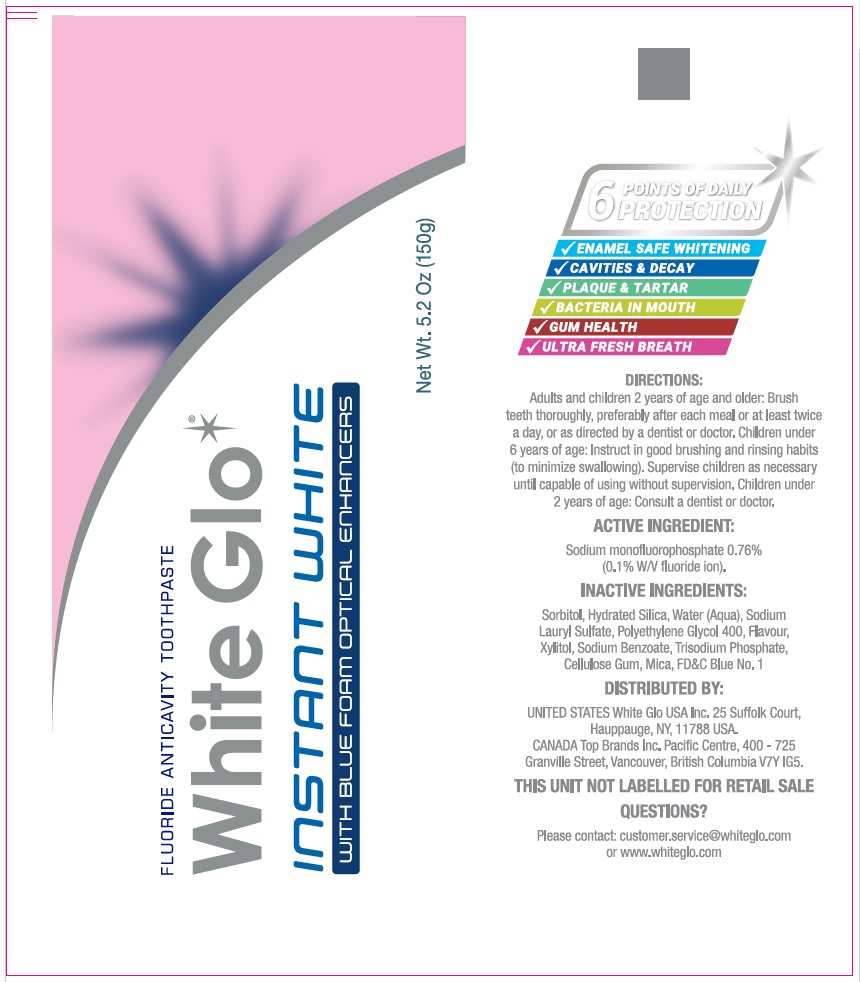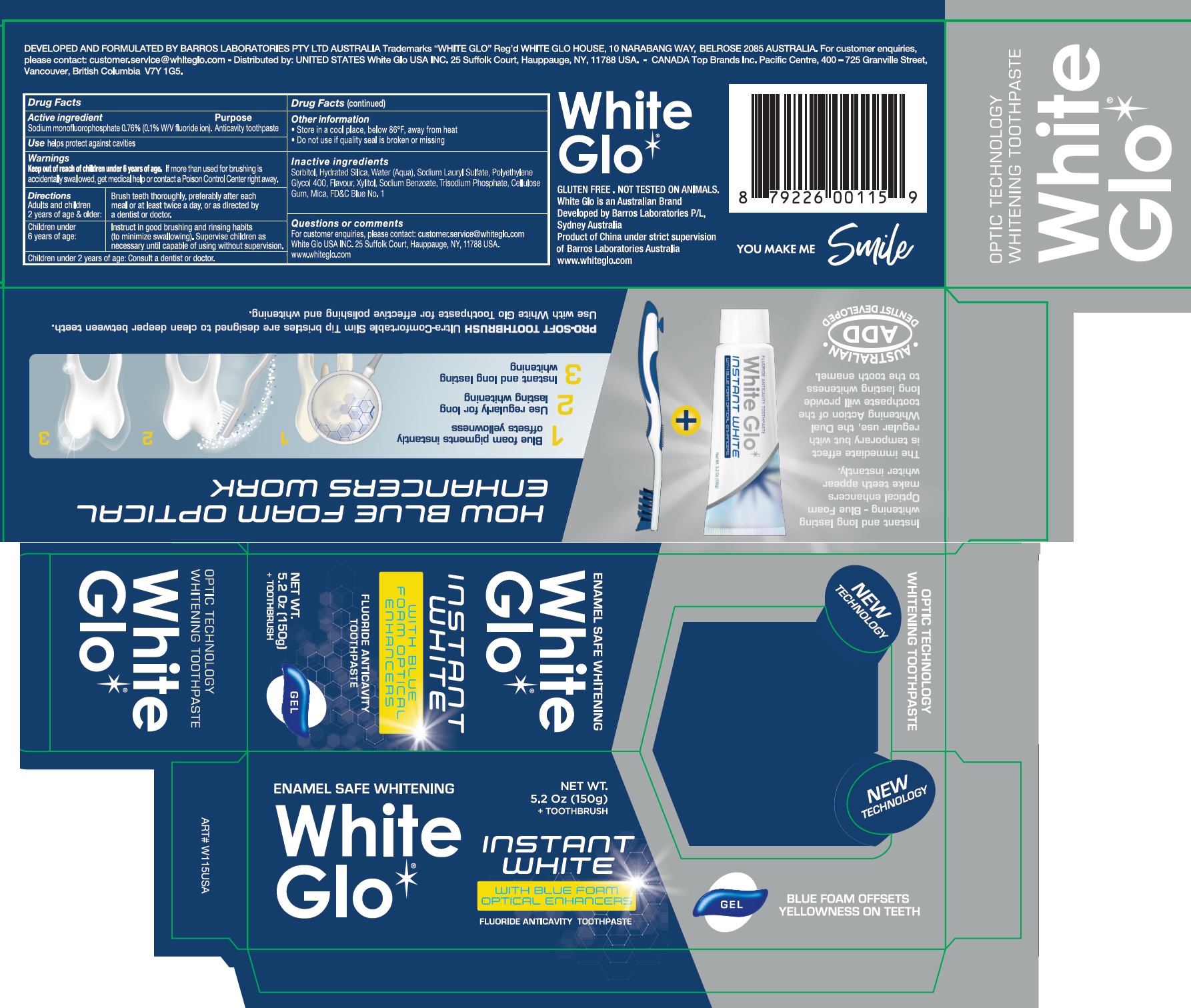 DRUG LABEL: White Glo Instant White
NDC: 73656-015 | Form: KIT | Route: DENTAL
Manufacturer: WHITE GLO USA INC
Category: otc | Type: HUMAN OTC DRUG LABEL
Date: 20250226

ACTIVE INGREDIENTS: SODIUM MONOFLUOROPHOSPHATE 0.001 mg/100 g
INACTIVE INGREDIENTS: SORBITOL; HYDRATED SILICA; WATER; SODIUM LAURYL SULFATE; POLYETHYLENE GLYCOL 400; XYLITOL; SODIUM BENZOATE; SODIUM PHOSPHATE, TRIBASIC, ANHYDROUS; CARBOXYMETHYLCELLULOSE SODIUM, UNSPECIFIED; MICA; FD&C BLUE NO. 1

White Glo Toothpaste Instant White + Toothbrush

Active ingredient

Sodium monofluorophosphate 0.76%(0.1% W/V fluoride ion)

Purpose

Anticavity toothpaste

Use

helps pretect against cavities

Warnings

Keep out of reach of children

If more than used for brushing is accidentally swallowed, get medical help or contact a Poison Control Center rightaway. under 6 years of age.

Directions

Adults and children 2 years of age & older: | Brush teeth thoroughly, preferably after each meal or at least twice a day, or as directed by a dentist or doctor.
Children under 6 years of age: | Instruct in good brushing and rinsing habits (to minimize swallowing). Supervise children as necessary until capable of using without supervision.

Children under 2 years of age: Consult a dentist or doctor.

Other information

- Store in a cool place, below 86°F, away from heat
- Do not use if quality seal is broken or missing

Inactive ingredients

Sorbitol, Hydrated Silica, Water (Aqua), Sodium Lauryl Sulfate, Polyethylene Glycol 400, Flavor, Xylitol, Sodium Benzoate, Tetrasodium Pyrophosphate, Cellulose Gum, Mica, FD&C Blue No.1

Questions or comments

For customer enquiries, please contact:customer.service@whiteglo.com White Glo USA INC. 25 Suffolk Court, Hauppauge, NY, 11788 USA. www.whiteglo.com